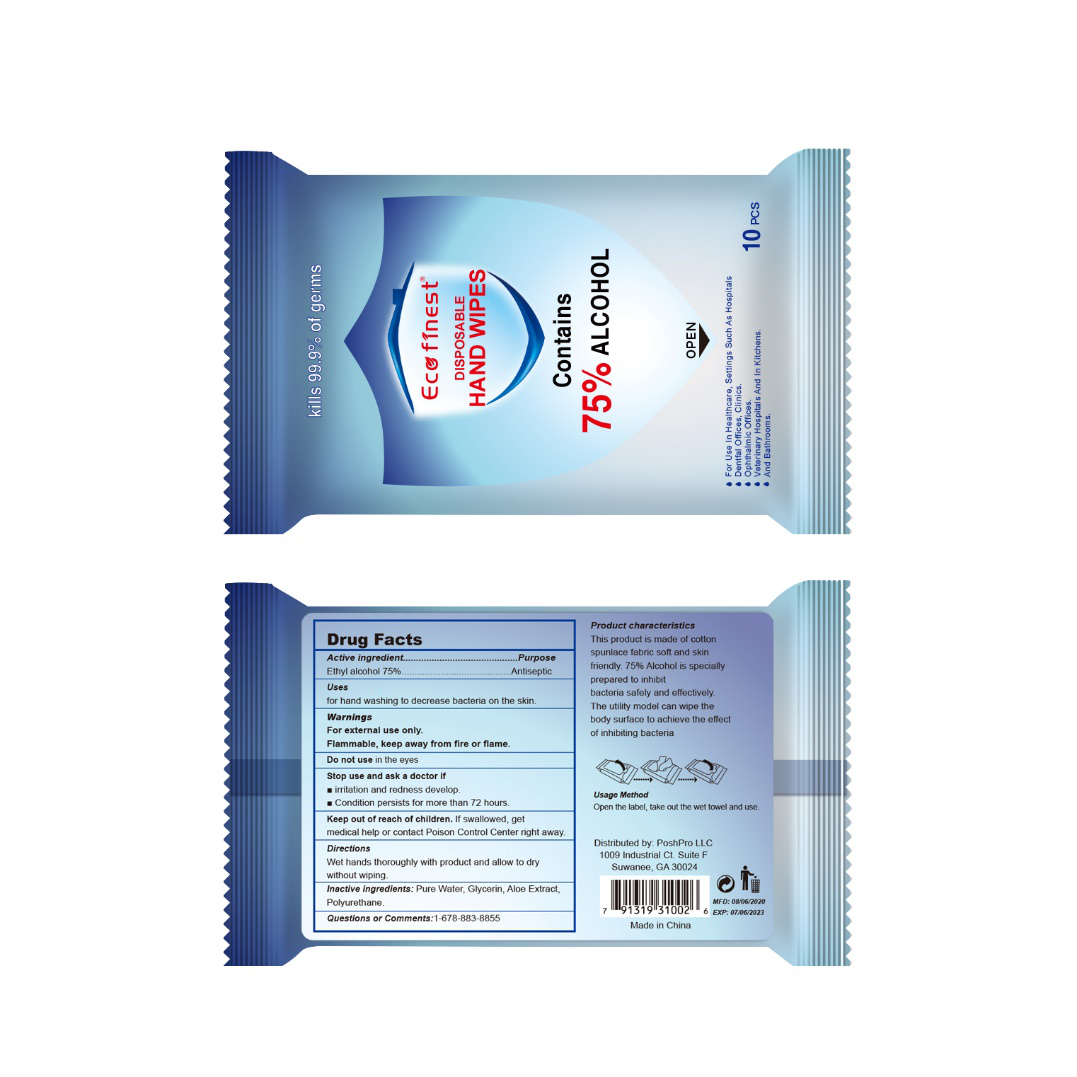 DRUG LABEL: Alcohol Wipes
NDC: 54237-007 | Form: CLOTH
Manufacturer: Guangzhou Daieme Cosmetic Co,.Ltd
Category: otc | Type: HUMAN OTC DRUG LABEL
Date: 20200828

ACTIVE INGREDIENTS: ALCOHOL 75 mL/10 1
INACTIVE INGREDIENTS: ALOE; GLYCERIN; POLYURETHANE-34 (40 MPA, TENSILE STRENGTH OF FILM AT BREAK); WATER

DOSAGE AND ADMINISTRATION

Place it in a cool and dry place, avoid direct sunlight and fire

ACTIVE INGREDIENT

Alcohol

keep out of reach of children

WARNINGS

Alcohol is volatile ,Please use it as so0n as possible after opening.Place it in a cool and dry place, avoid direct sunlight and fire,and avoid children eating by mistake.Please keep out of the reach of children,Avold contact with eyes and damaged skin.

INACTIVE INGREDIENT

Glycerin，Aloe Extract, Polyurethane, Non-woven Fabric，Water

PURPOSE

Disinfection
Sterilization
No Rinseing

INDICATIONS AND USAGE

open the label, Take out the wet towel and use.